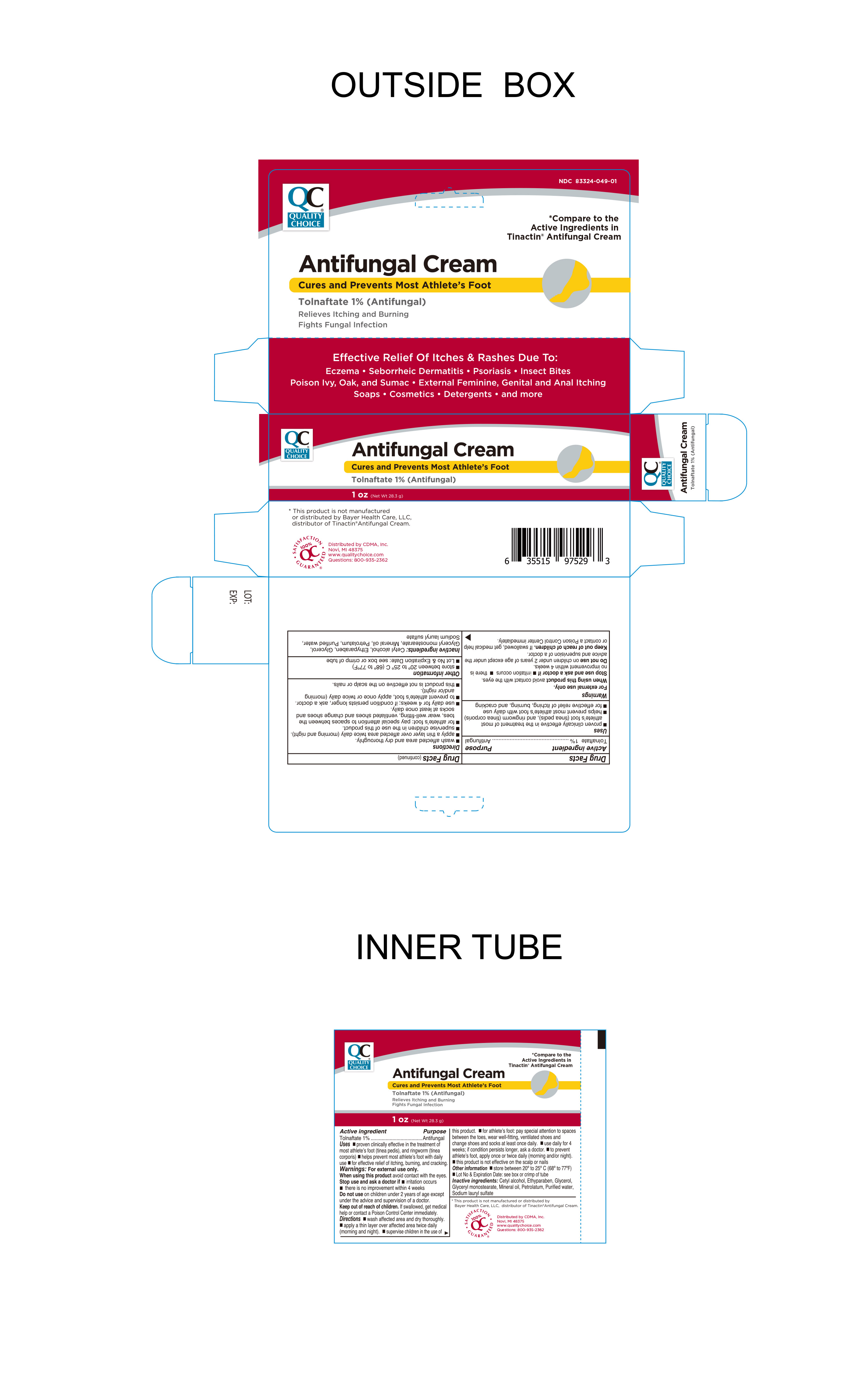 DRUG LABEL: Antifungal
NDC: 83324-049 | Form: CREAM
Manufacturer: Chain Drug Marketing Association Inc.
Category: otc | Type: HUMAN OTC DRUG LABEL
Date: 20241105

ACTIVE INGREDIENTS: TOLNAFTATE 1 g/100 g
INACTIVE INGREDIENTS: MINERAL OIL; ETHYLPARABEN; GLYCERIN; SODIUM LAURYL SULFATE; GLYCERYL MONOSTEARATE; PETROLATUM; WATER; CETYL ALCOHOL

Quality Choice Antifungal Cream Tolnaftate 1%

Active ingredient

Tolnaftate 1%

Purpose

Antifungal

Keep out of reach of children

If swallowed, get medical help or contact a Poison Control Center immediately.

Uses

● proven clinically effective in the treatment of most athlete's foot (tinea pedis), and ringworm (tinea corporis) ● helps prevent most athlete's foot with daily use ● for effective relief of itching, burning and cracking.

Warnings

For external use only.

When using this productavoid contact with the eyes.

Stop use and ask a doctorl if● irritation occurs ● there is no improvement within 4 weeks improvement

Do not use on children under 2 years of age except under the advice and supervision of a doctor.

Directions

● wash affected area and dry thoroughly

● apply a thin layer over affected area twice daily (morning and night)

● supervise children in the use of this product

● for athlete’s foot: pay special attention to spaces between the toes, wear well-fitting ventilated shoes and change shoes and socks at least once daily.

● use daily for 4 weeks; if conditions persists longer, ask a doctor.

● to prevent athlete's foot, apply once or twice daily (morning and/or night)

● this product is not effective on the scalp or nails.

Inactive ingredients

Cetyl alcohol, ethylparaben, glycerol, mineral oil, glycerol monostearate, petrolatum, purified water, sodium lauryl sulfate

Other information

● store between 20° to 25°C (68° to 77°F) ● Lot No & Expiration Date: See box or crimp of tube.

Distributed By

Distributed by CDMA, Inc.

Novi, MI. 48375

www.qualitychoice.com

Questions 800-935-2362

This product is not manufactured or distributed by Bayer Health Care, LLC. distributor of Tinactin® Antifungal Cream.